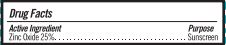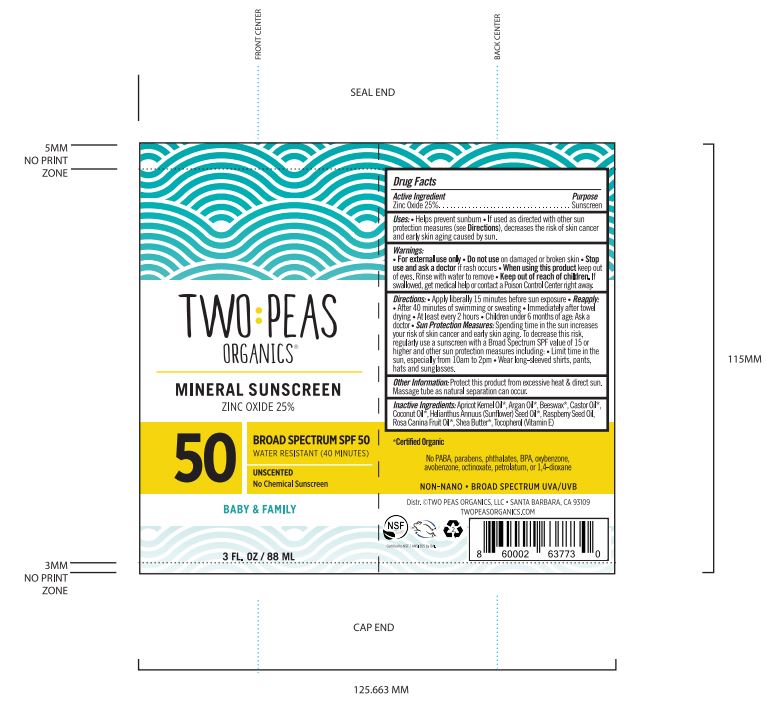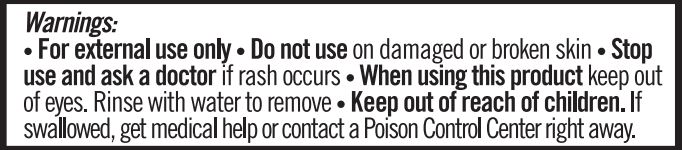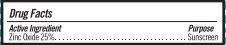 DRUG LABEL: SUNSCREEN
NDC: 62932-253 | Form: OINTMENT
Manufacturer: Private Label Select Ltd CO
Category: otc | Type: HUMAN OTC DRUG LABEL
Date: 20220104

ACTIVE INGREDIENTS: ZINC OXIDE 25 g/100 g
INACTIVE INGREDIENTS: WHITE WAX; .BETA.-TOCOPHEROL; SUNFLOWER OIL; CASTOR OIL; RASPBERRY SEED OIL; APRICOT KERNEL OIL; .GAMMA.-TOCOPHEROL; COCONUT OIL; SHEA BUTTER; ARGAN OIL; ROSA CANINA SEED; .ALPHA.-TOCOPHEROL, D-; .DELTA.-TOCOPHEROL

Two Peas Mineral Sunscreen, SPF 50